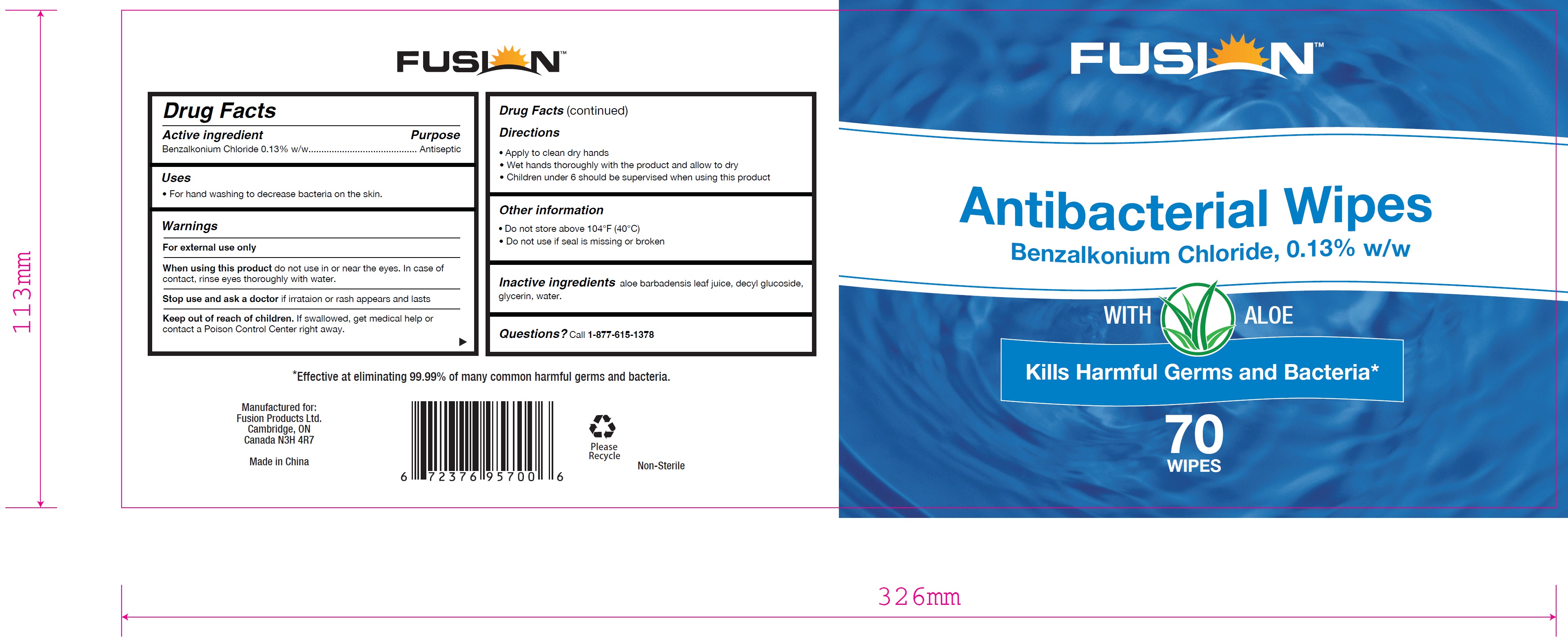 DRUG LABEL: Fusion Antibacterial Wipes
NDC: 80336-004 | Form: CLOTH
Manufacturer: Fusion Products Ltd.
Category: otc | Type: HUMAN OTC DRUG LABEL
Date: 20210629

ACTIVE INGREDIENTS: BENZALKONIUM CHLORIDE 0.0013 1/1 1
INACTIVE INGREDIENTS: WATER; GLYCERIN; ALOE VERA LEAF; DECYL GLUCOSIDE

Fusion Antibacterial Wipes

Active ingredient

Benzalkonium Chloride 0.13% w/w

Purpose

Antiseptic

Uses

For hand washing to decrease bacteria on the skin.

Warnings

For external use only

When using this product do not use in or near the eyes. In case of contact, rinse eyes thoroughly with water.

Stop use and ask a doctor if irritation or rash appears and lasts

Keep out of reach of children. If swallowed, get medical help or contact a Poison Control Center right away.

When using this product do not use in or near the eyes. In case of contact, rinse eyes thoroughly with water.

Stop use and ask a doctor if irritation or rash appears and lasts

Keep out of reach of children. If swallowed, get medical help or contact a Poison Control Center right away.

Directions

Apply to clean dry hands.

Wet hands thoroughly with the product and allow to dry

Children under 6 should be supervised when using this product

Other information

Do not store above 104°F (40°C)

Do not use if seal is missing or broken

Inactive Ingredients

aloe barbadensis leaf juice, decyl glucoside, glycerin, water.

PACKAGE LABEL

70 WIPES, NDC: 80336-004-09